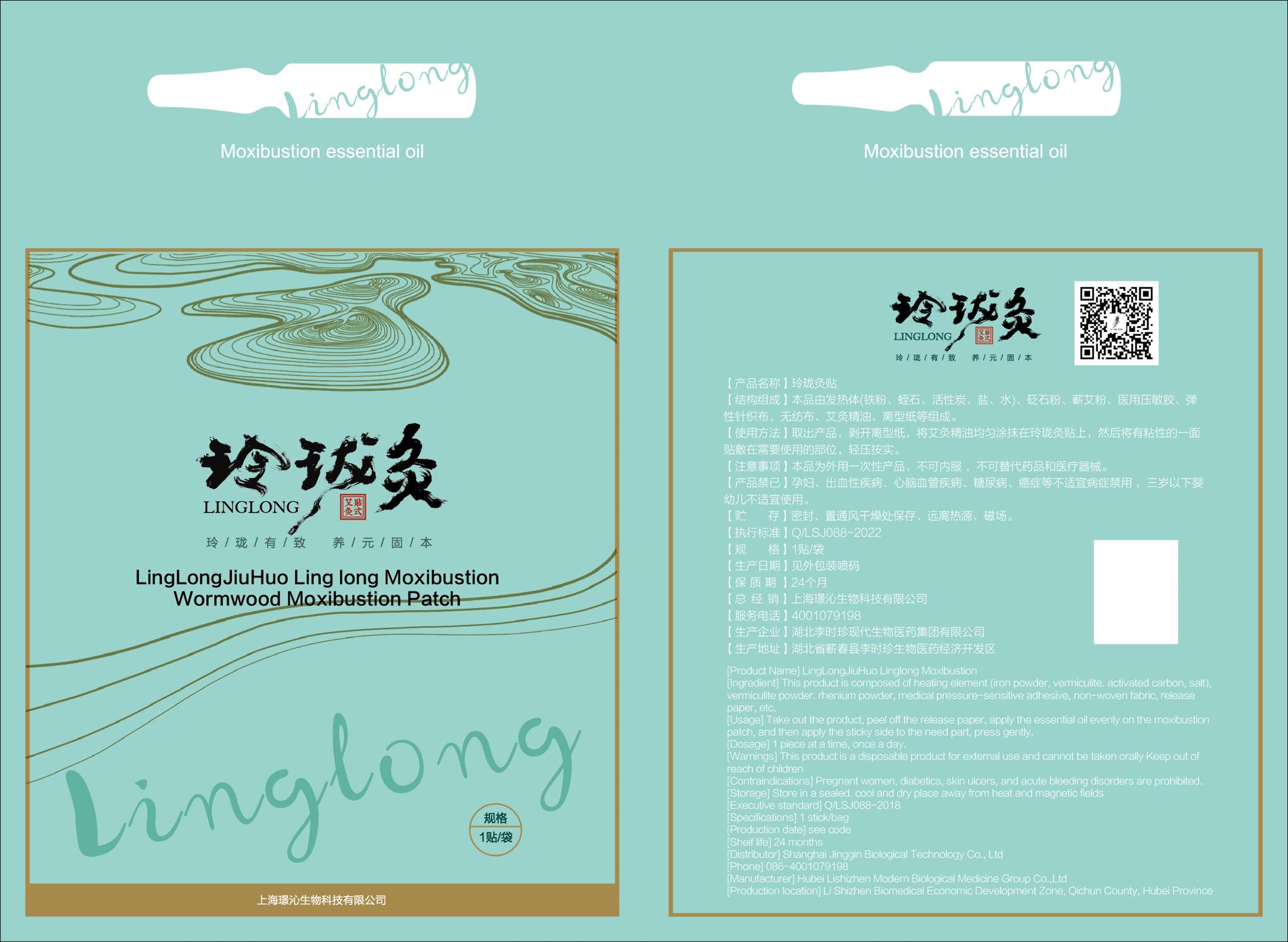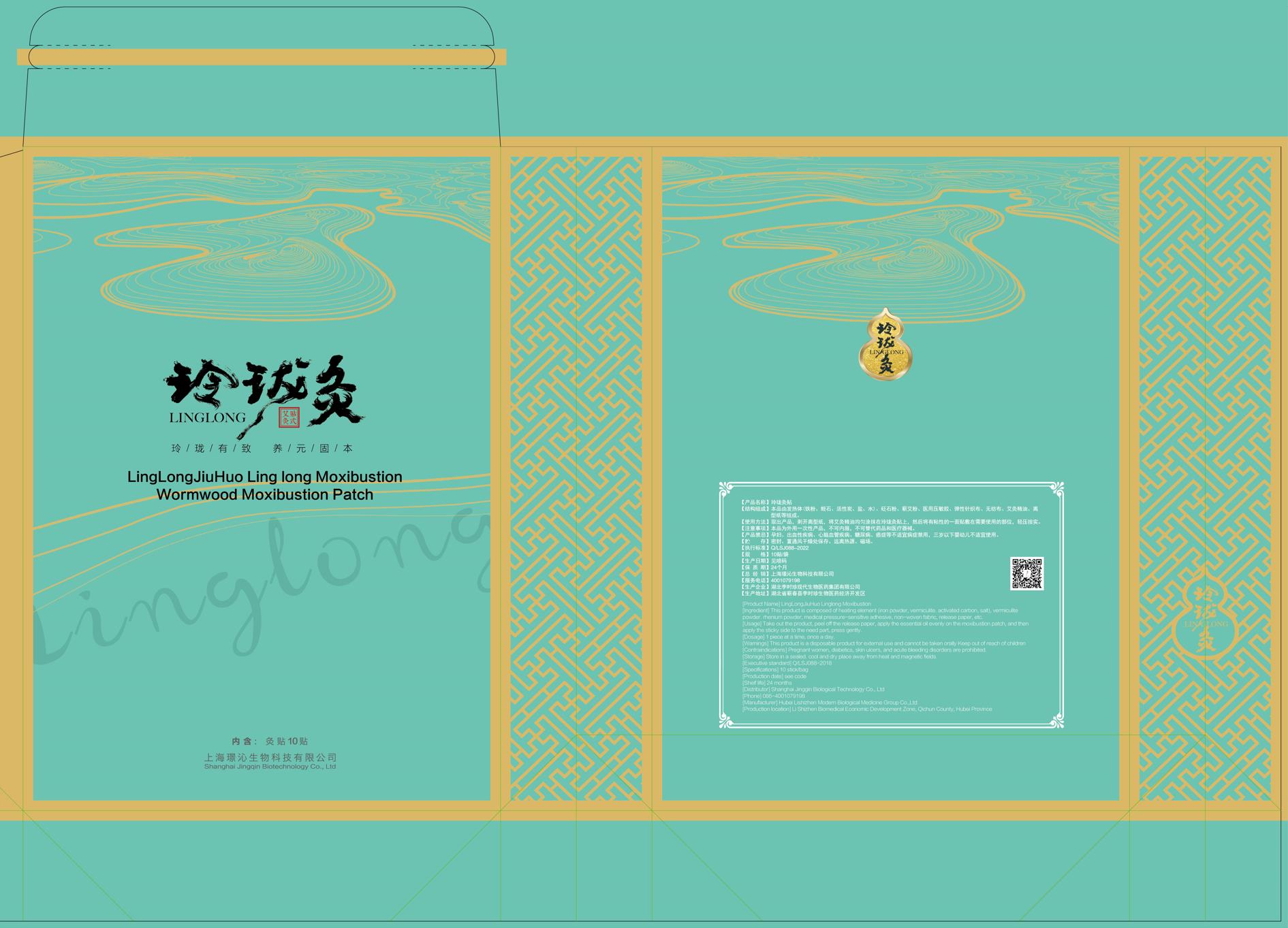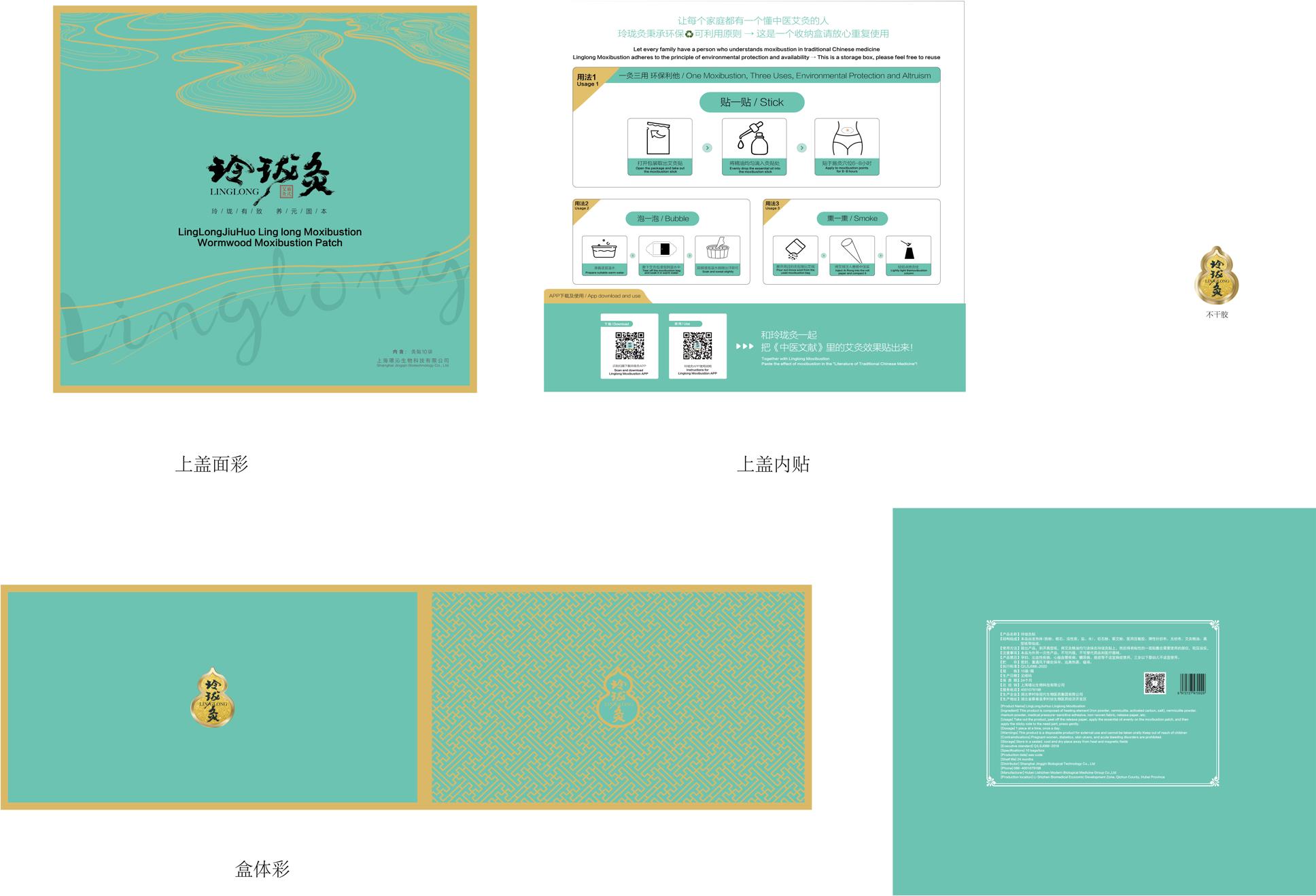 DRUG LABEL: LingLongJiuHuo Linglong Moxibustion Wormwood Moxibustion Patch
NDC: 73510-526 | Form: TAPE
Manufacturer: Shanghai Jingqin Biological Technology Co., Ltd.
Category: otc | Type: HUMAN OTC DRUG LABEL
Date: 20221015

ACTIVE INGREDIENTS: BUTYLENE GLYCOL 0.2 g/1 g
INACTIVE INGREDIENTS: HYDROXYETHYL CELLULOSE (280 MPA.S AT 2%); WATER; PHENOXYETHANOL; POLYETHYLENE GLYCOL 300000; CHLORPHENESIN

LingLongJiuHuo Linglong Moxibustion, JingQin

Active ingredient

butylene glycol 20% w/w

Inactive ingredient

water

hydroxyethylcellulose

polyethylene glycol 300000

phenoxyethanol

chlorphenesin

Purpose

It is a heat disposable paster incorporating chemicals that provides heat therapy for body.

When using

Conditioning neck, back, hands and feet and other rheumatism pain and spleen and stomach caused by cold injury, deficiency diarrhea and other conditions.

Do not use

Pregnant women, diabetics, skin ulcers, and acute bleeding disorders are prohibited.

Stop use

If irritation or discomfort occurs, discontinue the use and consult a physician.

Ask doctor

If irritation or discomfort occurs, discontinue the use and consult a physician.

Ask doctor/pharmacist when you current use other drugs.

Keep out of reach of children and away from eyes and ears.

Questions

Please contact with us at the phone number on the package when you have any questions.

Pregnancy or breast feeding

Pregnant or breast feeding women shall follow doctor advice.

Indications & usage

Pain relief, hot release, warming uterus, hemostatic, can be used to improve the conditioning neck, back, hands and feet and other rheumatism pain and spleen and stomach caused by cold injury, deficiency diarrhea and other conditions.

Dosage & administration

1 piece at a time; once a day.

Dosage forms & strengths

Its dosage form is patch.

1 piece at a time; once a day.

The active ingredient strength is 20% w/w.

Warnings

[Warnings] This product is a disposable product for external use and cannot be taken orally. Keep out of reach of children.

[Contraindications] Pregnant women, diabetics, skin ulcers, and acute bleeding disorders are prohibited.